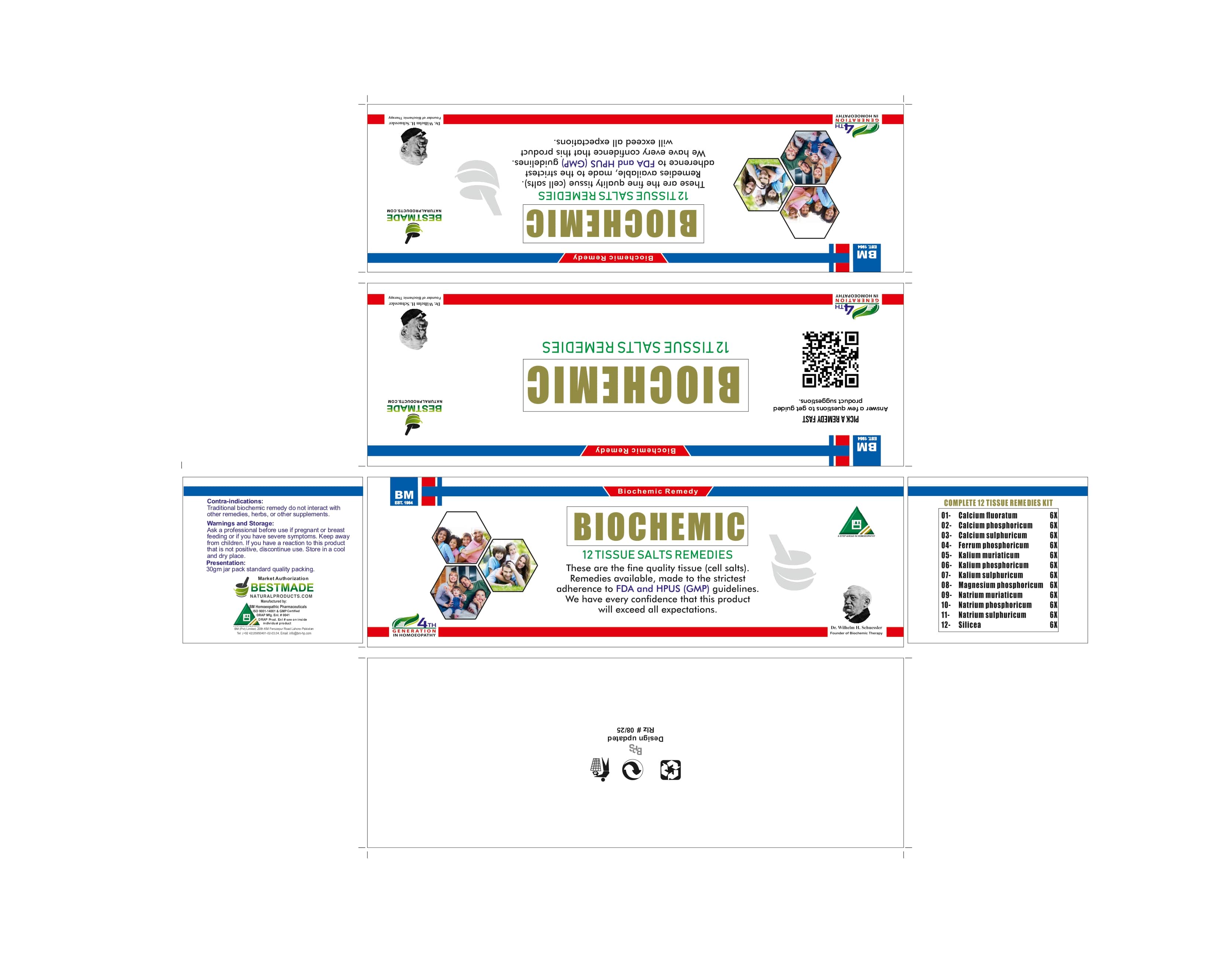 DRUG LABEL: Biochemic Tissue Salt Kit
NDC: 85816-1201 | Form: KIT | Route: ORAL
Manufacturer: BM Private Limited
Category: homeopathic | Type: HUMAN OTC DRUG LABEL
Date: 20251203

ACTIVE INGREDIENTS: POTASSIUM SULFATE 6 [hp_X]/60 mg; MAGNESIUM PHOSPHATE, DIBASIC TRIHYDRATE 6 [hp_X]/60 mg; FERROSOFERRIC PHOSPHATE 6 [hp_X]/60 mg; SODIUM CHLORIDE 6 [hp_X]/60 mg; SODIUM PHOSPHATE, DIBASIC, HEPTAHYDRATE 6 [hp_X]/60 mg; CALCIUM FLUORIDE 6 [hp_X]/60 mg; TRIBASIC CALCIUM PHOSPHATE 6 [hp_X]/60 mg; POTASSIUM CHLORIDE 6 [hp_X]/60 mg; POTASSIUM PHOSPHATE, DIBASIC 6 [hp_X]/60 mg; SODIUM SULFATE 6 [hp_X]/60 mg; SILICON DIOXIDE 6 [hp_X]/60 mg; CALCIUM SULFATE ANHYDROUS 6 [hp_X]/60 mg
INACTIVE INGREDIENTS: MAGNESIUM STEARATE 1.25 mg/60 mg; LACTOSE 58.6 mg/60 mg; MAGNESIUM STEARATE 1.25 mg/60 mg; LACTOSE 58.6 mg/60 mg; MAGNESIUM STEARATE 1.25 mg/60 mg; LACTOSE 58.6 mg/60 mg; MAGNESIUM STEARATE 1.25 mg/60 mg; LACTOSE 58.6 mg/60 mg; MAGNESIUM STEARATE 1.25 mg/60 mg; LACTOSE 58.6 mg/60 mg; MAGNESIUM STEARATE 1.25 mg/60 mg; LACTOSE 58.6 mg/60 mg; MAGNESIUM STEARATE 1.25 mg/60 mg; LACTOSE 58.6 mg/60 mg; MAGNESIUM STEARATE 1.25 mg/60 mg; LACTOSE 58.6 mg/60 mg; MAGNESIUM STEARATE 1.25 mg/60 mg; LACTOSE 58.6 mg/60 mg; MAGNESIUM STEARATE 1.25 mg/60 mg; LACTOSE 58.6 mg/60 mg; MAGNESIUM STEARATE 1.25 mg/60 mg; LACTOSE 58.6 mg/60 mg; MAGNESIUM STEARATE 1.25 mg/60 mg; LACTOSE 58.6 mg/60 mg

BM Biochemic Cell Salt Kit

INACTIVE INGREDIENT

Lactose, magnesium stearate

ACTIVE INGREDIENT

Calc Fluor
Calc Phos
Calc Sulph
Ferr Phos
Kali Mur
Kali Phos
Kali Sulph
Mag Phos
Nat Mur
Nat Phos
Nat Sulph
Silicea

Warnings and Storage:

Ask a professional before use if pregnant or breastfeeding, or if you have severe symptoms. Keep away from children. If you have a reaction to this product that is not positive, discontinue use. Store in a cool and dry place.

DOSAGE AND ADMINISTRATION

See individual product directions for use.

INDICATIONS AND USAGE

Temporarily boost cellular nutrition, satisfy mineral imbalances in the body, and stimulate the body's natural healing process

PURPOSE

Temporarily boost cellular nutrition, satisfy mineral imbalances in the body, and stimulate the body's natural healing process.

Warnings:

Keep out of reach of children.

PACKAGE LABEL

box